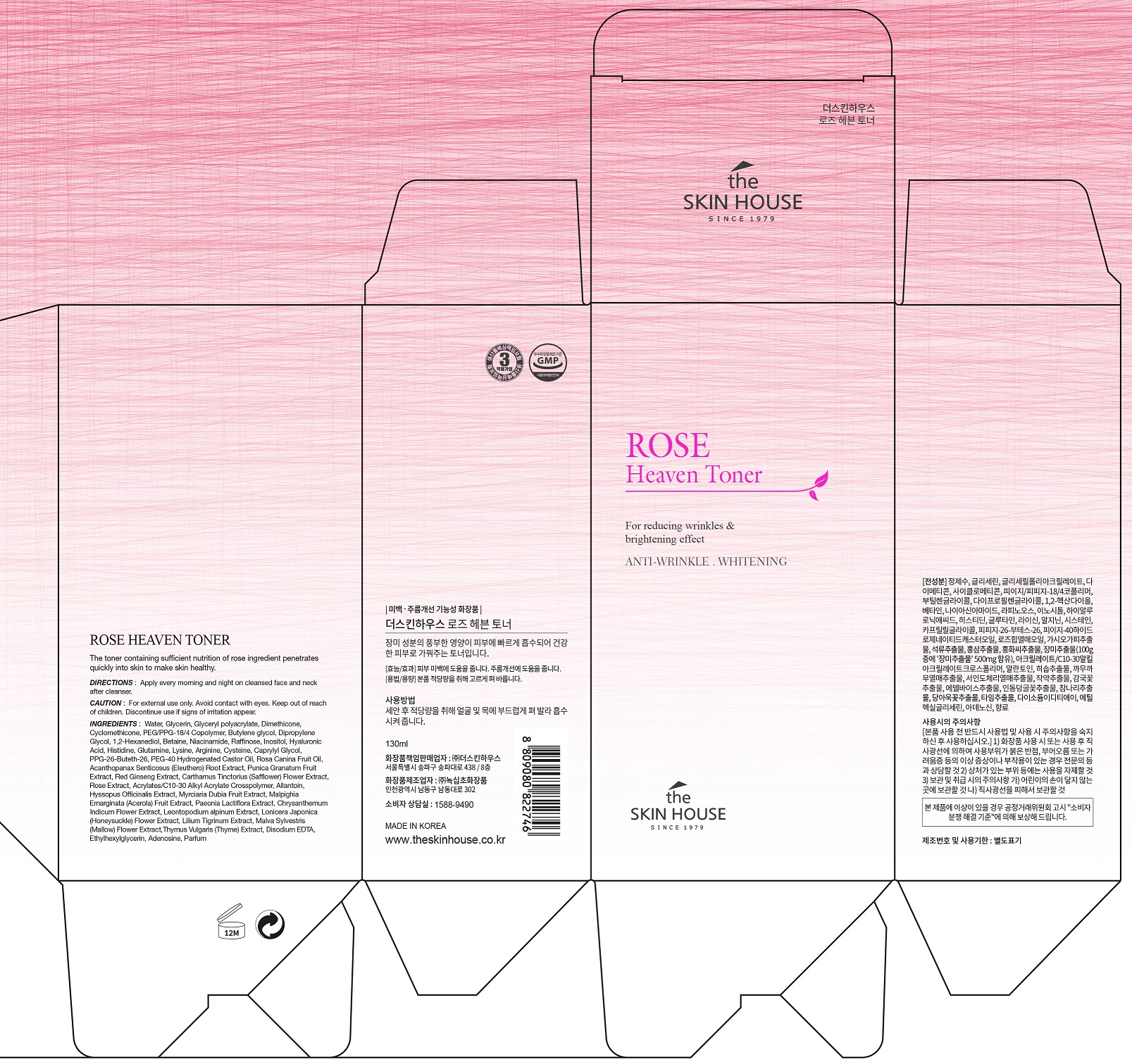 DRUG LABEL: THE SKINHOUSE Rose Heaven Toner
NDC: 73590-0009 | Form: LIQUID
Manufacturer: NOKSIBCHO cosmetic Co., Ltd.
Category: otc | Type: HUMAN OTC DRUG LABEL
Date: 20200307

ACTIVE INGREDIENTS: LEONTOPODIUM ALPINUM FLOWER 0.1 g/100 mL; NIACINAMIDE 2 g/100 mL; ADENOSINE 0.04 g/100 mL; ROSA CANINA FRUIT 0.5 g/100 mL; ROSA CANINA FRUIT OIL 0.5 g/100 mL; PAEONIA LACTIFLORA WHOLE 0.1 g/100 mL
INACTIVE INGREDIENTS: WATER

Drug Facts

ACTIVE INGREDIENT

Rose Extract, Rosa Canina Fruit Oil, Paeonia Lactiflora Bark/Sap Extract, Leontopodium Alpinum extract, Adenosine, Niacinamide

INACTIVE INGREDIENT

Water
Glycerin
PEG/PPG-18/4 Copolymer
Butylene glycol
Glyceryl polyacrylate
Dipropylene Glycol
1,2-Hexanediol
Betaine
Raffinose
Inositol
Sodium Hyaluronate
Histidine
Glutamine
Lysine
Cysteine
Caprylyl Glycol
PPG-26-Buteth-26
PEG-40 Hydrogenated Castor Oil
osa Canina Fruit Oil
Acanthopanax Senticosus (Eleuthero) Root Extract
Punica Granatum Fruit Extract
Panax Ginseng Root Extract
Carthamus Tinctorius (Safflower) Flower Extract
Propylene Glycol
Red ginseng extract
Acrylates/C10-30 Alkyl Acrylate Crosspolymer
Arginine
Cyclomethicone
Allantoin
Hyssopus Officinalis Extract
Myrciaria Dubia
Fruit Extract
Malpighia Emarginata
(Acerola) Fruit Extract
Chrysanthemum Indicum Flower Extract
Leontopodium alpinum extract
Lonicera Japonica (Honeysuckle) Flower Extract
Lilium Tigrinum Extract
Malva Sylvestris (Mallow) Flower Extract
Thymus Vulgaris (Thyme) Extract
Phenoxy ethanol
Disodium EDTA
Ethylhexylglycerin
Adenosine
Parfum

PURPOSE

- Anti-aging & brightening toner

A U-shape clear essence toner enables the skin to become nutritious.

Rose extracts, rose hips oil and other 14 kinds of natural extracts make the dehydrated skin to become moist, bright, smooth and more vital. Skin can absorb the toner without leaving stickiness and the toner gives a energy to skin instantly. Also, the delicate rose-scented gives elegant and classy feelings.

It is a toner which strengthens the autogenic power of skin.

keep out of reach of the children

INDICATIONS AND USAGE

1. After cleansing, wet a cotton pad with enough toner and apply it on your face.

2. Apply it softly from the center part of your face to the outer part along the skin texture.

3. Pat your face to be absorbed completely.

WARNINGS

For external use only
When using this product

■ if the following symptoms occurs after use, stop use and consult with a skin specialist

red specks, swelling, itching

■ don’t use on the part where there is injury, eczema, or dermatitis

Keep out of reach of children

■ if swallowed, get medical help or contact a person control center immediately